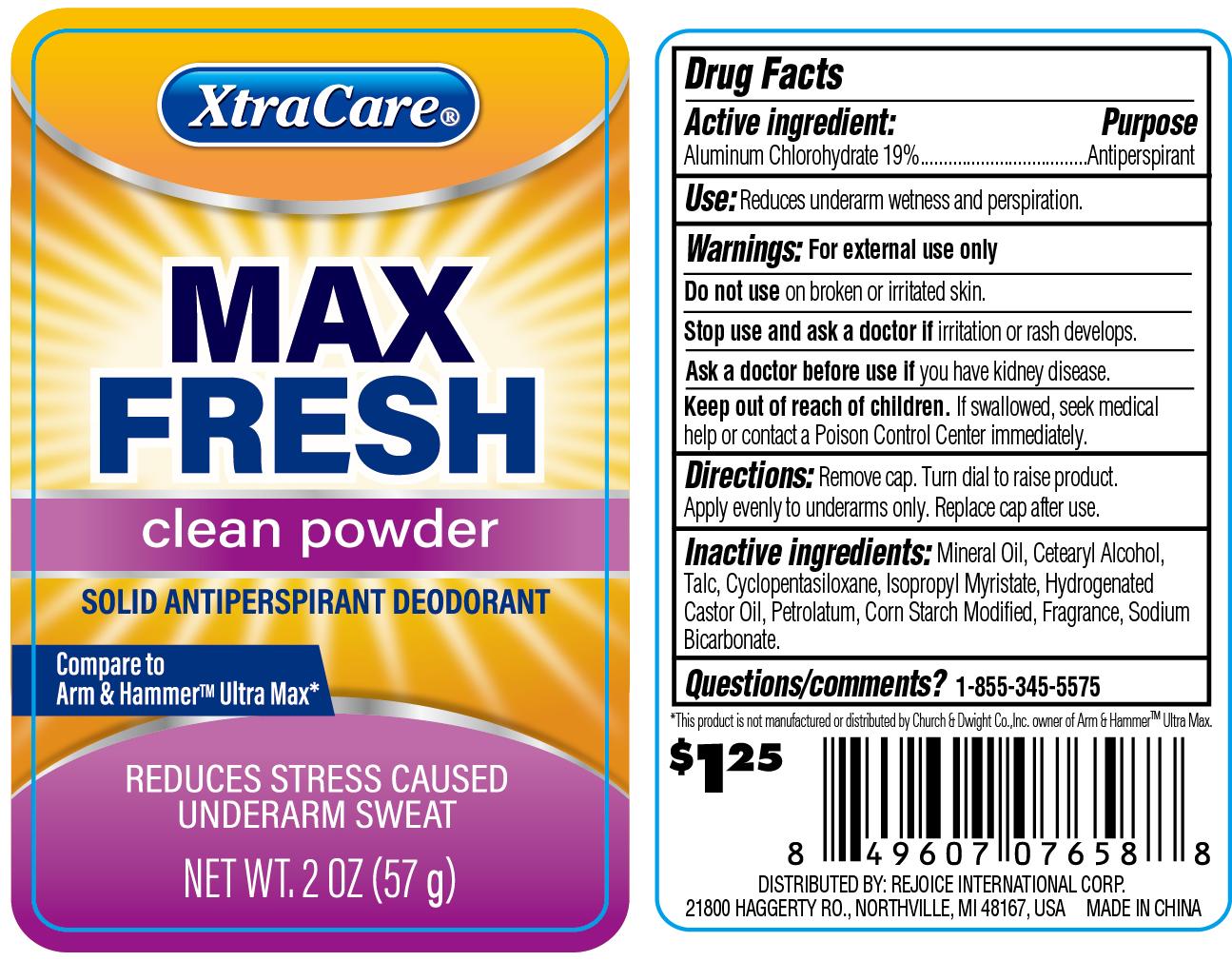 DRUG LABEL: Antiperspirant Deodorant Clean Powder 2oz
NDC: 58503-209 | Form: POWDER
Manufacturer: China Ningbo Shangge Cosmetics Technology Corp.
Category: otc | Type: HUMAN OTC DRUG LABEL
Date: 20260105

ACTIVE INGREDIENTS: ALUMINUM CHLOROHYDRATE 19 g/100 g
INACTIVE INGREDIENTS: TALC; HYDROGENATED CASTOR OIL; MINERAL OIL; STARCH, CORN; CETOSTEARYL ALCOHOL; PETROLATUM; SODIUM BICARBONATE; CYCLOMETHICONE 5; ISOPROPYL MYRISTATE

07658# Antiperspirant Deodorant Clean Powder 2oz
08219# Antiperspirant Deodorant Clean Powder 1.6oz

Active ingredient

Aluminum Chlorohydrate 19%

Purpose

Antiperspirant

Use

Reduces underarm wetness and perspiration.

Warnings

For external use only

Do not use on broken or irritated skin.

Stop use and ask a doctor if irritation or rash develops.

Ask a doctor before use if you have kidney disease.

Keep out of reach of children

If swallowed, seek medical help or contact a Poison Control Center immediately.

Directions

Remove cap. Turn dial to raise product. Apply evenly to underarm only. Replace cap after use.

Inactive ingredients

Mineral Oil
Cetearyl Alcohol
Talc
Cyclopentasiloxane
Isopropyl Myristate
Hydrogenated Castor Oil
Petrolatum
Corn Starch Modified
Fragrance
Sodium Bicarbonate